DRUG LABEL: Unknown
Manufacturer: Mallinckrodt Inc.
Category: prescription | Type: HUMAN PRESCRIPTION DRUG LABELING
Date: 20071001

NEUTROSPECTM
Kit for the Preparation of Technetium (99m Tc) fanolesomab

Diagnostic Radiopharmaceutical
For intravenous use only
Rx ONLY
CONTAINS SODIUM HYDROSULFITE

DESCRIPTION

NeutroSpecTM [Kit for the Preparation of Technetium (99m Tc) fanolesomab] is a radiodiagnostic agent consisting of a murine IgM monoclonal antibody, formulated to be labeled with technetium Tc 99m. Each NeutroSpecTM kit contains all the excipients needed to reconstitute and to radiolabel this imaging agent with sodium pertechnetate Tc 99m Injection, USP. The murine monoclonal antibody fanolesomab is produced in suspension culture of hybridoma cells. NeutroSpecTM [Technetium (99m Tc) fanolesomab] is an in vivo diagnostic radiopharmaceutical that can be visualized by nuclear medicine instrumentation.

Each NeutroSpecTM kit contains a single use vial of fanolesomab as a sterile, non-pyrogenic, lyophilized mixture of 0.25 mg fanolesomab; 12.5 mg maltose monohydrate; 0.522 mg sodium potassium tartrate tetrahydrate, USP; 0.221 mg succinic acid; 54 mcg stannous tartrate (minimum stannous 7 mcg; maximum total stannous and stannic tin 24 mcg); 28 mcg glycine, USP; and 9.3 mcg disodium edetate dihydrate, USP. The lyophilized powder contains no preservatives and has no US standard of potency.

When sterile, pyrogen-free sodium pertechnetate Tc 99m Injection, USP in isotonic saline (no preservatives) is added to the single use fanolesomab vial, a Tc 99m complex of fanolesomab is formed with an approximate pH of 6.2.

Physical Characteristics of Technetium Tc 99m

Technetium 99m decays by isomeric transition with a physical half-life of 6.02 hours. The photon that is useful for imaging studies is listed in Table 1.

Table 1. Principal radiation emission data for technetium Tc 99m
Radiation | Mean Percent per Disintegration | Mean Energy (keV)
Gamma-2 | 89.07 | 140.5

External Radiation

The specific gamma-ray constant for technetium Tc 99m is 5.4 μC·kg^-1·MBq^-1·h^-1 (0.78 R/mCi·h) at 1 cm. The first half-value thickness of lead for Tc 99m is 0.017 cm. A range of values for the relative attenuation of the radiation emitted by this radionuclide that results from the interposition of various thicknesses of lead is shown in Table 2. For example, the use of a 0.25 cm thickness of lead will decrease the external radiation exposure by a factor of 1,000.

Table 2. Radiation attenuation by lead shielding
Lead Shield Thickness (cm) | Coefficient of Attenuation
0.017 | 0.5
0.08 | 0.1
0.16 | 0.01
0.25 | 0.001
0.33 | 0.0001

To correct for physical decay of this radionuclide, the fractions that remain at selected time intervals after the time of calibration are shown in Table 3.

Table 3. Physical decay chart—technetium Tc 99m half-life 6.02 hours
Hours | Fraction Remaining | Hours | Fraction Remaining
0* | 1.00 | 7 | 0.45
1 | 0.89 | 8 | 0.40
2 | 0.79 | 9 | 0.36
3 | 0.71 | 10 | 0.32
4 | 0.63 | 11 | 0.28
5 | 0.56 | 12 | 0.25
6 | 0.50 | 18 | 0.13
*Calibration Time (time of preparation)

CLINICAL PHARMACOLOGY

Pharmacodynamics

Fanolesomab is directed against the carbohydrate moiety 3-fucosyl-N-acetyllactosamine that defines the cluster of differentiation 15 (CD15) antigen. NeutroSpecTM [Technetium (99m Tc) fanolesomab] radiolabels human white blood cells and myeloid precursors. The CD15 antigen is expressed on the surface of polymorphonuclear neutrophils (PMNs), eosinophils and monocytes. Monocytes and eosinophils constitute approximately 5% of circulating leukocytes; therefore, most of the circulating blood cellular activity resides on PMNs. In blood cell fractions isolated from healthy volunteers who had received NeutroSpecTM, radioactivity was associated with PMNs (25%) or plasma (72%) when measured one hour after injection. The binding of fanolesomab to its antigenic sites on human PMNs has an apparent Kd = 1.6 × 10^-11 M.

Cross-reactivity studies indicate the presence of CD15 antigenic sites on many human tissues.

Pharmacokinetics

In a study of 10 healthy volunteers, following intravenous injection of NeutroSpecTM, blood concentrations of radioactivity decreased rapidly with an initial half-life of 0.3 hours and a second phase half-life of approximately eight hours. Whole-body scintigraphy at two hours post-injection indicated that the liver had the highest radioactivity uptake and retention (50% of the injected dose), followed by the kidney, spleen and red marrow. Over the 26–33 hours after injection, 38% of the injected dose of radioactivity was recovered in urine.

CLINICAL STUDIES

A multicenter, single-arm study evaluated 200 patients (5 to 86 years of age) with equivocal signs and symptoms of appendicitis defined as absence of one or more of the following: periumbilical pain migrating to right lower quadrant (RLQ), gradual onset of pain, increasing intensity of pain over time, pain aggravated by movement and coughing, McBurney's point tenderness, referred tenderness to RLQ with palpation in other quadrants, abdominal muscular spasm with RLQ tenderness, temperature > 101^0 F, white blood cell count > 10,500/mm^3. Readers blinded to clinical information (except for age, gender and body habitus) assessed the diagnosis of appendicitis by NeutroSpecTM imaging. The diagnosis by the blinded readers was compared with a final clinical diagnosis based upon a surgical pathology report (in cases that proceeded to appendectomy) or upon two weeks of follow-up (in cases without surgical intervention). The study investigators had access to other diagnostic modalities (e.g., CT scan and ultrasound) and were instructed not to rely on NeutroSpecTM imaging for their diagnosis of appendicitis. Appendicitis prevalence in this study was 30%. The image evaluation was limited to the assessment of the planar images performed in specified projections at defined time points and single photon emission tomography was not used to assess performance in this study.

The performance rates for the diagnosis of appendicitis by the blinded readers and by the clinical investigators are shown in Table 4.

Table 4. Diagnostic performance of NeutroSpecTM
 | Performance Rates (n=200)
Evaluation | Blinded Readers percentages (95%CI) | Study Investigators percentages(95%CI)
Sensitivity | 75 (62, 85) | 91 (80, 97)
Specificity | 93 (87, 97) | 86 (79, 91)
Accuracy | 87 (82, 92) | 87 (81, 91)
Positive Predictive Value | 82 (69, 91) | 74 (62, 84)
Negative Predictive Value | 90 (84, 94) | 96 (90, 99)

In a supportive single-arm, two-center study of the detection of appendicitis in 56 patients of whom 50% had a final diagnosis of appendicitis, the diagnostic performance of NeutroSpecTM was similar to the performance observed in the larger study.

Other intra-abdominal conditions

Among 30 study patients with other types of intra-abdominal infection (surgical and non-surgical), 13 scintigrams were read as positive for appendicitis.

INDICATIONS AND USAGE

NeutroSpecTM [Technetium (99m Tc) fanolesomab] is indicated for scintigraphic imaging of patients with equivocal signs and symptoms of appendicitis who are five years of age or older.

CONTRAINDICATIONS

NeutroSpecTM should not be administered to patients who are hypersensitive to any murine proteins or other component of the product.

WARNINGS

Hypersensitivity Reactions

Allergic reactions, including anaphylaxis, can occur in patients who receive murine antibodies such as fanolesomab.

CenolateTM Ascorbic Acid, USP injection (diluent) contains sodium hydrosulfite, a sulfite that may cause allergic reactions, including anaphylaxis. Serious hypersensitivity reactions were not observed in the 523 patients who received NeutroSpecTM in the clinical studies. Emergency resuscitation personnel and equipment for the treatment of hypersensitivity reactions should be immediately available during administration of this agent.

PRECAUTIONS

Repeat Administration

NeutroSpecTM has not been studied in repeat administration to patients. Murine monoclonal antibodies are frequently immunogenic. The development of human anti-mouse antibodies (HAMA) can alter the pharmacokinetics, biodistribution, safety, and imaging performance properties of the administered agent.

Use in Patients with Neutropenia

The biodistribution and the imaging performance of NeutroSpecTM in neutropenic patients have not been studied. NeutroSpecTM induces transient neutropenia and a downward shift in white blood cell counts. (See ADVERSE REACTIONS Laboratory Values). The safety and effectiveness of NeutroSpecTM in patients with neutropenia have not been established.

General Use and Handling

NeutroSpecTM [Technetium (99m Tc) fanolesomab], like other radioactive medical products, must be handled with care and appropriate safety measures should be used to minimize radiation exposure to clinical personnel. Care should also be taken to minimize radiation exposure to the patient consistent with proper patient management.

Radiopharmaceuticals should be used by or under the control of personnel who are qualified by specific training and experience in the safe use and handling of radionuclides, and whose experience and training have been approved by the appropriate governmental agency authorized to license the use of radionuclides.

Information for patients

Murine monoclonal antibodies such as fanolesomab are foreign proteins and their administration can induce hypersensitivity reactions. Patients should be informed that the use of this product could affect their future use of other murine based products, and should be advised to discuss prior use of murine antibody based products with their health care provider.

To minimize the radiation-absorbed dose to the bladder, adequate hydration should be encouraged to permit frequent voiding during the first few hours after injection. To help protect themselves and others in their environment, patients should take the following precautions for 12 hours after injection. Whenever possible, a toilet should be used, rather than a urinal and the toilet should be flushed several times after each use. Spilled urine should be cleaned up completely. After each voiding or fecal elimination, patients should thoroughly wash their hands. If blood, urine or feces soil clothing, the clothing should be washed separately.

Carcinogenesis, Mutagenesis, Impairment of Fertility

Studies have not been conducted to evaluate carcinogenic potential, mutagenic potential, or effects on fertility.

Pregnancy

Pregnancy Category C. Animal reproductive studies have not been conducted with NeutroSpecTM. It is also not known whether NeutroSpecTM can cause fetal harm when administered to a pregnant woman or can affect reproductive capacity. NeutroSpecTM should not be used during pregnancy unless the potential benefit to the patient justifies the potential risk to the fetus.

Nursing Mothers

It is not known whether this drug is excreted in human milk. Because many drugs are excreted in human milk, caution should be exercised when NeutroSpecTM is administered to a nursing woman. Whenever possible, infant formula should be substituted for breast milk until the radioactivity has cleared from the body of the nursing woman.

Pediatric Use

In clinical studies of NeutroSpecTM, 29 (5%) patients were 5–11 years old and 32 (6%) were 12–16 years old. No overall differences in safety or effectiveness were observed between these patients and patients in other age brackets, however, this number of patients is too few to exclude differences.

Geriatric Use

In clinical studies of NeutroSpecTM, 64 (12%) patients were 65 years or older. No overall differences in safety or effectiveness were observed between these patients and younger patients, but this number of patients is too few to exclude differences.

ADVERSE REACTIONS

The data described below reflect exposure to NeutroSpecTM in 523 patients and normal volunteers receiving a mean antibody dose of 121 mcg (33–250 mcg) and a mean radioactive dose of 15 mCi (1-33 mCi). The median patient age was 35 years (5-91 years); 53% of patients were women and 61% of patients were Caucasians.

Two patients enrolled in studies of post surgical infection or abscess had serious adverse events associated with fatality (hypotension and worsening of sepsis). Underlying medical conditions may have also contributed to the fatality and the relationship of the fatality to NeutroSpec™ cannot be determined.

Overall, 49 adverse events occurred in 37 (7%) of the 523 patients exposed to NeutroSpecTM. Four of these events were classified as severe (hypotension, worsening of sepsis, chest pressure and decreased SaO2, pain). The most frequently reported adverse events were flushing (n=10, 2%) and dyspnea (n=5, 1%). Other less common adverse events (< 1%) included syncope, dizziness, hypotension, chest pressure, paresthesia, nausea, injection site burning/erythema, pain, and headache.

Because clinical trials are conducted under widely varying controlled conditions, adverse reaction rates observed in clinical trials of a drug cannot be directly compared with rates in the clinical trials of another drug, and may not reflect the rates observed in practice. The adverse reaction information from clinical trials does, however, provide a basis for identifying the adverse events that appear to be related to drug use and for approximating rates.

Laboratory Test Values

NeutroSpecTM induced transient decreases in neutrophil counts in a study of 10 healthy volunteers. Neutrophil counts began to decrease within 3 to 5 minutes post-injection and returned to pre-injection values within four hours. Downward shifts in neutrophil counts have been observed in 18% of patients (28/151). Three of 284 patients were observed to develop transient elevations of AST and ALT after NeutroSpecTM administration.

Immunogenicity

The incidence of antibody development in patients receiving NeutroSpecTM has not been adequately determined because the assay was not directly quantitative and its ability to detect low titers could not be assured. Human anti-mouse antibody (HAMA) response following a single NeutroSpecTM administration was evaluated in a total of 54 patients 3-16 weeks post injection. None of the patients had a positive HAMA response. In 30 healthy volunteers who were exposed to two administrations of fanolesomab separated by two weeks, fanolesomab induced HAMA response in five volunteers.

Immunogenicity data are highly dependent on the sensitivity and specificity of the assay. Additionally, the observed incidence of antibody positivity in an assay may be influenced by several factors, including sample handling, timing of sample collection, concomitant medications, and underlying disease. For these reasons, comparison of the incidence of antibodies to NeutroSpecTM with the incidence of antibodies to other products may be misleading.

OVERDOSAGE

There is no experience with overdosage in clinical trials.

DOSAGE AND ADMINISTRATION

Adults

To prepare NeutroSpecTM the reaction vial containing fanolesomab is reconstituted with sodium pertechnetate Tc 99m Injection, USP solution prior to use. (See INSTRUCTIONS FOR PREPARATION).

Fanolesomab is not intended for direct administration to the patient without reconstitution and labeling with sodium pertechnetate Tc 99m Injection, USP. NeutroSpecTM [Technetium (99m Tc) fanolesomab] is intended for a single intravenous (IV) administration through an intravenous access that has been demonstrated to be patent, e.g., butterfly, running IV line, or equivalent injection system to assure that no dose infiltration occurs. Following administration, flush the injection line with an appropriate volume of saline to assure administration of the total dose.

For imaging, 75 to 125 mcg of fanolesomab is labeled with 10 to 20 mCi (370 to 740 MBq) and administered as a single dose of NeutroSpecTM.

Planar imaging should be performed using a large field of view camera fitted with a low-energy, parallel-hole, high-resolution collimator. The camera should be positioned so that the lower edge of the liver is at the upper end of the field of view at the midline of the patient.

Dynamic image acquisition over the lower abdomen should begin at the time of injection and consist of 10 sequential four-minute images. Following dynamic image acquisition, the patient should ambulate for approximately 10 to 15 minutes and void. Static planar images should then be collected, including supine anterior, posterior, 10–25 degree RAO and LAO views of the lower abdomen, followed by a standing anterior image of the lower abdomen. After the camera has been positioned (as described above), it is recommended that a total of one million counts be collected for the anterior supine image. All remaining images should be collected for the same duration of time required for the anterior supine image.

Children (Five years and older)

NeutroSpecTM is administered in a single dose of 0.21 mCi/kg to a maximum of 20 mCi. Recommended imaging times and procedures are the same as for adults.

Dose adjustment has not been established in patients with renal insufficiency, in geriatric patients or in pediatric patients under five years of age.

Image Interpretation

The biodistribution of the NeutroSpecTM radiopharmaceutical is imaged in the blood pool, reticuloendothelial system (liver, spleen, bone marrow), and urinary excretion organs (kidneys and urinary tract). Imaging of the uterus has been noted, consistent with blood pool activity of NeutroSpecTM.

In the 200-patient clinical trial (see CLINICAL STUDIES), based on the average of the three blinded reader interpretations, 75% of the 59 true positive cases of appendicitis were identified (range 66-81%).

Among those with a blinded diagnosis of appendicitis, 76% displayed uptake of radiotracer activity in the appendix within 30 minutes following injection and 98% did so by 60 minutes following injection.

In the trial the acquisition of image collection was performed for a 90 minute period. The image finding of a persistent or intensifying uptake in the right lower quadrant (appendix zone) that is seen before the completion of the entire imaging sequence may be considered a positive study, and imaging may be terminated at this time. In the case of a negative image finding at 30 and 60 minutes, collection to 90 minutes is recommended prior to termination of the study.

A diagnostic abnormality is characterized by the presence of an irregular, asymmetric uptake of radiotracer localized in the right lower quadrant of the abdomen. The abnormal localization of radiotracer remains constant or increases in intensity in follow up imaging.

RADIATION DOSIMETRY

Based on human data, the absorbed radiation dose to an average human adult (70 kg) from an intravenous injection of NeutroSpecTM is listed in Table 5. The values were calculated using the Standard Medical Internal Radiation Dosimetry (MIRD) method. The values are listed as rad/mCi and mGy/MBq and assume urinary bladder emptying at 4.8 hours. Radiation absorbed dose estimates for children are given in Table 6.

Table 5. Absorbed radiation dose in adults (NeutroSpecTM)
Target Organ | rad/mCi | mGy/MBq
Spleen | 0.23 | 0.062
Kidneys | 0.19 | 0.051
Liver | 0.18 | 0.048
Urinary Bladder Wall | 0.12 | 0.032
Heart | 0.061 | 0.017
Gallbladder | 0.056 | 0.015
Upper Large Intestine Wall | 0.051 | 0.014
Adrenal Glands | 0.044 | 0.012
Lungs | 0.043 | 0.012
Thyroid Gland | 0.042 | 0.011
Red Marrow | 0.038 | 0.010
Lower Large Intestine Wall | 0.034 | 0.0091
Bone Surface | 0.031 | 0.0083
Brain | 0.0052 | 0.0014
Testes / Ovaries | 0.0039 / 0.019 | 0.0010 / 0.0052
Total Body | 0.019 | 0.0050
Dose calculations were performed using the standard MIRD method (MIRD Pamphlet No. 1 rev., Soc. Nucl. Med., 1976). Effective dose equivalent was calculated in accordance with ICRP 53 (Ann. ICRP 18, 1-4, 1988) and gave a value of 0.018 mSv/MBq (0.068 rem/mCi).

Table 6. Estimated absorbed radiation dose for a five-year old child
Target Organ | rad/mCi | mGy/MBq
Spleen | 0.70 | 0.19
Kidneys | 0.43 | 0.11
Liver | 0.41 | 0.11
Urinary Bladder Wall | 0.27 | 0.072
Upper Large Intestine Wall | 0.21 | 0.056
Thyroid Gland | 0.19 | 0.052
Lower Large Intestine Wall | 0.16 | 0.042
Heart | 0.15 | 0.041
Gallbladder | 0.13 | 0.036
Red Marrow | 0.11 | 0.030
Lungs | 0.11 | 0.028
Adrenal Glands | 0.095 | 0.026
Bone Surface | 0.085 | 0.023
Testes / Ovaries | 0.019 / 0.059 | 0.0052 / 0.016
Brain | 0.0075 | 0.0020
Total Body | 0.049 | 0.013
Dose calculations were performed using the standard MIRD method based upon biodistribution studies conducted in adults. Effective dose equivalent was calculated in accordance with ICRP 53 and gave a value of 0.047 mSv/MBq (0.17 rem/mCi).

USE ASEPTIC TECHNIQUE THROUGHOUT

The user should wear waterproof gloves during the entire procedure and while withdrawing the patient dose from the NeutroSpecTM vial.

Transfer Sodium Pertechnetate Tc 99m Injection, USP with an adequately shielded, sterile syringe.

Adequate shielding should be maintained at all times until the preparation is administered to the patient, disposed of in an approved manner, or allowed to decay to background levels. A shielded, sterile syringe should be used to withdraw and inject the labeled preparation.

Before reconstituting a vial, it should be inspected for cracks and any indication that the integrity of the vacuum seal has been lost. The material should not be used if integrity of the vacuum seal has been lost. After reconstitution, examine the vial contents for particulates and discoloration prior to injection. The material should not be used if particulates or discoloration are observed.

The dose should be injected via an indwelling catheter, butterfly, or equivalent injection system to assure that no dose infiltration occurs. Following administration, flush the injection line with an appropriate volume of saline to assure administration of the total dose.

Labeling and Preparation of NeutroSpecTM

1. Required Materials, Not Supplied within the NeutroSpecTM kit:
  1. Sodium Pertechnetate Tc-99m, USP, oxidant-free
  2. ITLC-SG Strips, Heat Treated
  3. Methyl Ethyl Ketone (MEK)
  4. Developing Chambers - 50 mL disposable tubes
  5. Pipettors and tips
  6. Forceps
  7. Gamma Counter
  8. Dose Calibrator
  9. Sodium Chloride for Injection, USP
  10. Alcohol (or Germicidal)
  11. Lead Shield
  12. 1 mL Sterile Syringes
  13. Water Bath stabilized at 37±1° C
2. Remove a fanolesomab reaction vial from refrigerated storage (2 to 8° C) and allow it to come to room temperature (usually 5 to 10 minutes). NOTE: Keep Cenolate ampule refrigerated and protected from light until needed (Step 5).
3. Swab the rubber stopper of the fanolesomab reaction vial with an appropriate antiseptic and allow the stopper to dry.
4. Aseptically add 20 to 40 mCi (740 to 1480 MBq) Sodium Pertechnetate Tc 99m Injection, USP in 0.20 to 0.35 mL generator eluate. Gently swirl (Do not shake) the vial until the lyophilized product is completely dissolved, ensuring the vial is not inverted.
  Cautionary Notes:
  - Use only eluate from a technetium Tc 99m generator that was previously eluted within the last 24 hours.
  - Technetium 99m eluate which is more than 8 hours old from the time of elution should NOT be used.
  - The amount of Sodium Pertechnetate Tc 99m Injection, USP used to reconstitute the reaction vial should be determined based on the desired radioactive dose and the estimated time of use.
  - If Sodium Pertechnetate Tc 99m Injection, USP must be diluted prior to kit reconstitution, only sterile sodium chloride for injection, USP, (without preservatives) should be used.
5. Incubate at 37º C for 30 minutes. (Shorter incubation times may result in inadequate labeling.)
6. Aseptically add sufficient CenolateTM [Ascorbic Acid Injection, USP (500 mg/mL)] to make the final preparation volume up to 1 mL.
  Note: Further dilution is not recommended.
7. Assay the product in a suitable calibrator and record the time, date of preparation and the activity of NeutroSpecTM onto the string tag label and attach to lead dispensing shield (“pig”).
8. Each patient should receive a dose of 10-20 mCi of NeutroSpecTM (the final reconstituted product).
9. Discard vials, needles and syringes in accordance with local, state, and federal regulations governing radioactive and biohazardous waste.

Recommended Method for Radiochemical Purity Testing

1. After addition of CenolateTM (Ascorbic Acid Injection, USP) aseptically withdraw approximately 10 μL of the final reconstituted product for Quality Control (QC) testing. Care should be taken not to introduce air into the vial. Use of a shielded 0.5 - 1.0 cc syringe with a 25 or 27 gauge needle is recommended.
2. Apply 1 - 5 μL (a drop that has not completely formed on the tip of a 25 - 27 gauge needle) of NeutroSpecTM 2 cm (origin) from the bottom of an ITLC-SG 1.5 x 10 cm strip and allow the solution to absorb into the strip (approximately 5 seconds).
3. Immediately place the strip, origin side down, in a development chamber containing 4 mL methyl ethyl ketone (MEK).
4. Allow the strip to develop until the solvent front is within 0.5 cm of the top of the strip (3 - 5 minutes).
5. Remove the strip using forceps and allow to dry.
6. Cut the strip at the 4 cm mark, place each piece in a separate counting tube and measure the radioactivity associated with each piece.
7. Calculate the % Free Technetium Tc 99m Pertechnetate as follows:

% Free Pertechnetate = | Radioactivity in Solvent Front Piece x 100%
 | Total Radioactivity in Strip

Note: The product should only be used if the percentage of Free Technetium Tc 99m Pertechnetate is ≤ 10%.

HOW SUPPLIED

NeutroSpecTM Kit for the Preparation of Technetium (99m Tc) fanolesomab

The NeutroSpecTM kit contains five individual kits each containing:

One | 3 mL single use vial of fanolesomab as a sterile, non-pyrogenic, lyophilized mixture of 0.25 mg fanolesomab; 12.5 mg maltose monohydrate; 0.522 mg sodium potassium tartrate tetrahydrate, USP; 0.221 mg succinic acid; 54 mcg stannous tartrate (minimum stannous 7 mcg; maximum total stannous and stannic tin 24 mcg); 28 mcg glycine, USP; and 9.3 mcg disodium edetate dihydrate, USP. The lyophilized powder contains no preservatives and has no US standard of potency.
One | 2 mL ampule CenolateTM [Ascorbic Acid Injection, USP (500 mg/mL)]
One | NeutroSpecTM Package Insert
One | String tag label for NeutroSpecTM vials (reconstituted product)

STORAGE

Refrigerate the lyophilized NeutroSpecTM kits at 2 to 8° C (36 to 46° F). After labeling with Sodium Pertechnetate Tc 99m Injection, USP and addition of CenolateTM (Ascorbic Acid injection, USP) the vial should be kept at room temperature, 15 to 25° C (46 to 77° F) and used within six hours. Use appropriate radiation shielding.

This reagent kit is approved for distribution to persons licensed by the U.S. Nuclear Regulatory Commission to use byproduct material identified in 10 CFR 35.200 or under an equivalent license issued by an Agreement State.

NeutroSpecTM is manufactured for Palatin Technologies, Inc., Cranbury, NJ 08512 by Ben Venue Laboratories, Inc., Bedford, OH 44146
U.S. Patent X,XXX,XXX
US license number 1588

CenolateTM (Ascorbic Acid Injection, USP) is manufactured for Palatin Technologies, Inc. by Hospira, Chicago, IL 60064

Distributed by:
Mallinckrodt Inc.
St. Louis, MO 63134

Rx only

Printed in USA
NeutroSpecTM is a registered trademark of Palatin Technologies, Inc.
Cenolate is a registered trademark of Hospira.